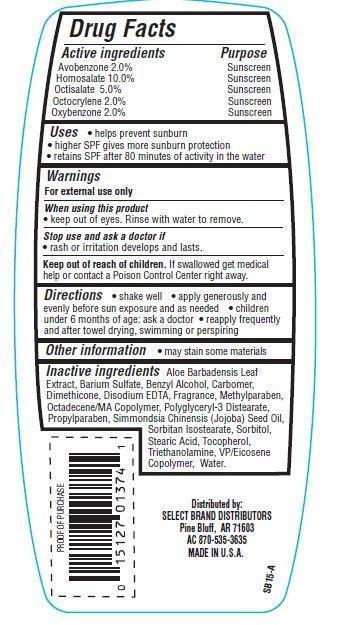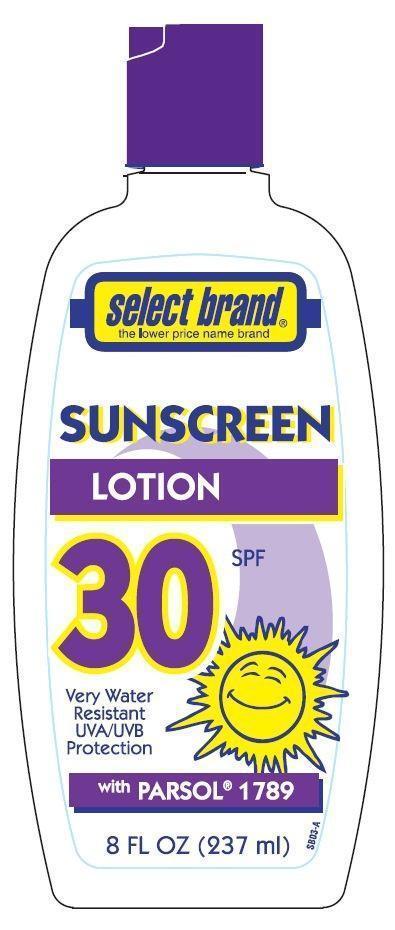 DRUG LABEL: Select Brand Sunscreen
                
NDC: 15127-005 | Form: LOTION
Manufacturer: Select Brand Distributors
Category: otc | Type: HUMAN OTC DRUG LABEL
Date: 20121121

ACTIVE INGREDIENTS: AVOBENZONE 2 g/100 g; HOMOSALATE 10 g/100 g; OCTISALATE 5 g/100 g; OCTOCRYLENE 2 g/100 g; OXYBENZONE 2 g/100 g
INACTIVE INGREDIENTS: BENZYL ALCOHOL; SORBITAN ISOSTEARATE; DIMETHICONE; METHYLPARABEN; TOCOPHEROL; PROPYLPARABEN; EDETATE DISODIUM; WATER; SORBITOL; TROLAMINE; STEARIC ACID; BARIUM SULFATE; ALOE VERA LEAF; JOJOBA OIL

Drug Facts

Active ingredients

Avobenzone 2.0%
Homosalate 10.0%
Octisalate 5.0%
Octocrylene 2.0%
Oxybenzone 2.0%

Purpose

Sunscreen

Uses

- helps prevent sunburn
- higher SPF gives more sunburn protection
- retains SPF after 80 minutes of activity in water

Warnings

For external use only

When using this product

- keep out of eyes. Rinse with water to remove.

Stop use and ask a doctor if

- rash or irritation develops and lasts.

Keep out of the reach of children.
If swallowed get medical help or contact a Poison Control Center right away.

Directions

- shake well
- apply generously and evenly before sun exposure and as needed
- children under 6 months of age: ask a doctor
- reapply frequently and after towel drying, swimming or perspiring

Other information

- may stain some materials

Inactive ingredients

Water, Sorbitan Isostearate, Sorbitol, Polyglyceryl-3 Distearate, Triethanolamine, Stearic Acid, VP/Eicosene Copolymer, Benzyl Alcohol, Dimethicone, Barium Sulfate, Carbomer, Simmondsia Chinensis (Jojoba) Seed Oil, Tocopherol, Disodium EDTA, Octadecene/MA Copolymer, Aloe Barbadensis Leaf Extract, Methylparaben, Propylparaben, Fragrance.

Principal Display Panel

select brand
the lower price name brand
SUNSCREEN LOTION
30 SPF
Very Water Resistant
UVA/UVB Protection
with PARSOL 1789
8 FL OZ(237 mL)